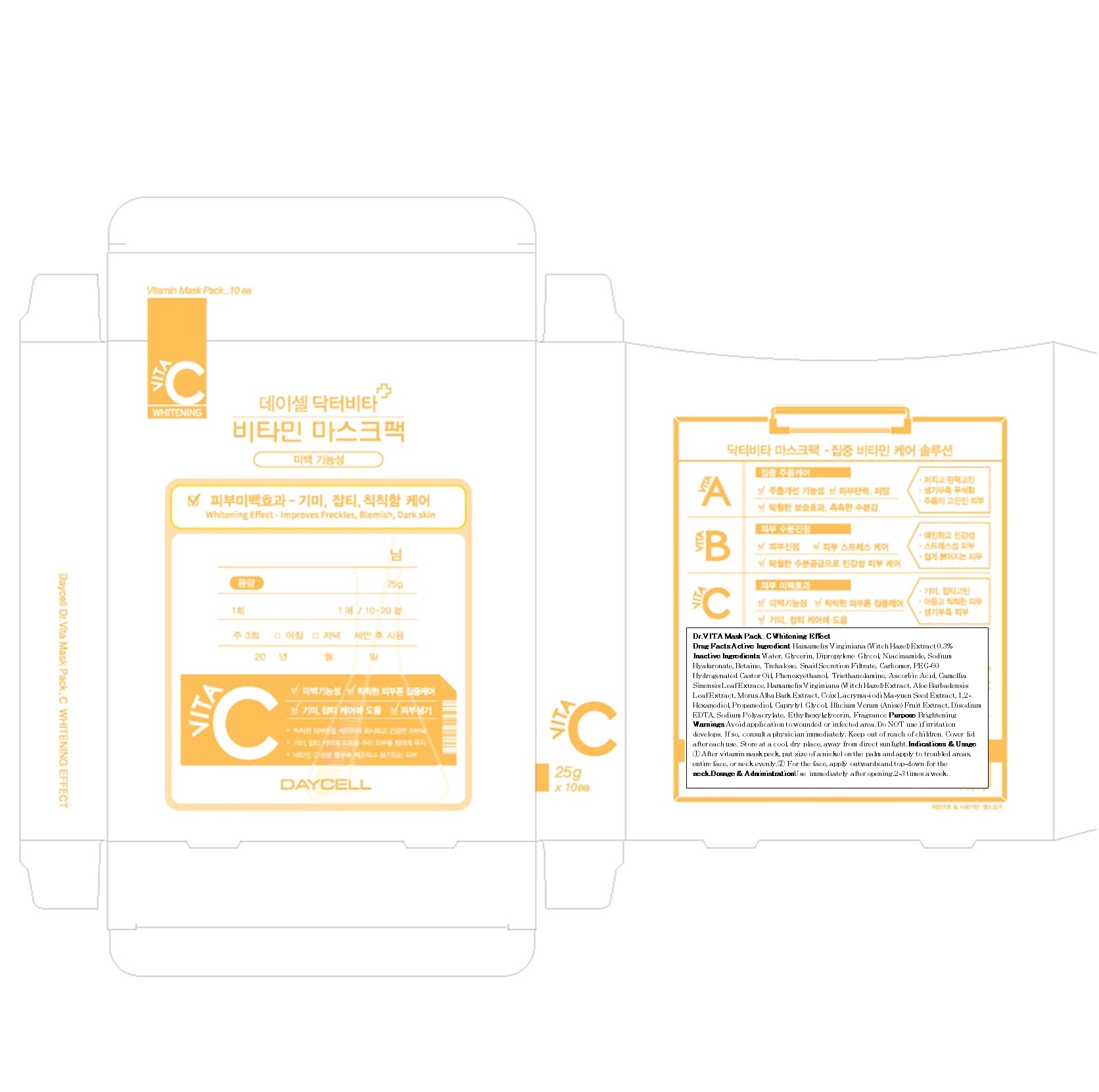 DRUG LABEL: Dr VITA Mask Pack C Whitening Effect
NDC: 70545-010 | Form: PATCH
Manufacturer: DAYCELL COSMETICS CO., LTD.
Category: otc | Type: HUMAN OTC DRUG LABEL
Date: 20160328

ACTIVE INGREDIENTS: Witch Hazel 0.07 g/10 1
INACTIVE INGREDIENTS: Water; Glycerin

ACTIVE INGREDIENT

Active Ingredient: Hamamelis Virginiana (Witch Hazel) Extract 0.3%

INACTIVE INGREDIENT

Inactive Ingredients: Water, Glycerin, Dipropylene Glycol, Niacinamide, Sodium Hyaluronate, Betaine, Trehalose, Snail Secretion Filtrate, Carbomer, PEG-60 Hydrogenated Castor Oil, Phenoxyethanol, Triethanolamine, Ascorbic Acid, Camellia Sinensis Leaf Extrace, Hamamelis Virginiana (Witch Hazel) Extract, Aloe Barbadensis Leaf Extract, Morus Alba Bark Extract, Coix Lacryma-jodi Ma-yuen Seed Extract, 1,2-Hexanediol, Propanediol, Caprylyl Glycol, Illicium Verum (Anise) Fruit Extract, Disodium EDTA, Sodium Polyacrylate, Ethylhexylglycerin, Fragrance

PURPOSE

Purpose: Brightening

WARNINGS

Warnings: Avoid application to wounded or infected area. Do NOT use if irritation develops. If so, consult a physician immediately. Keep out of reach of children. Cover lid after each use. Store at a cool, dry place, away from direct sunlight.

KEEP OUT OF REACH OF CHILDREN

INDICATIONS & USAGE

Indications & Usage: 1. After vitamin mask peck, put size of a nickel on the palm and apply to troubled areas, entire face, or neck evenly. 2. For the face, apply outwards and top-down for the neck.

DOSAGE & ADMINISTRATION

Dosage & Administration: Use immediately after opening. 2-3 times a week.